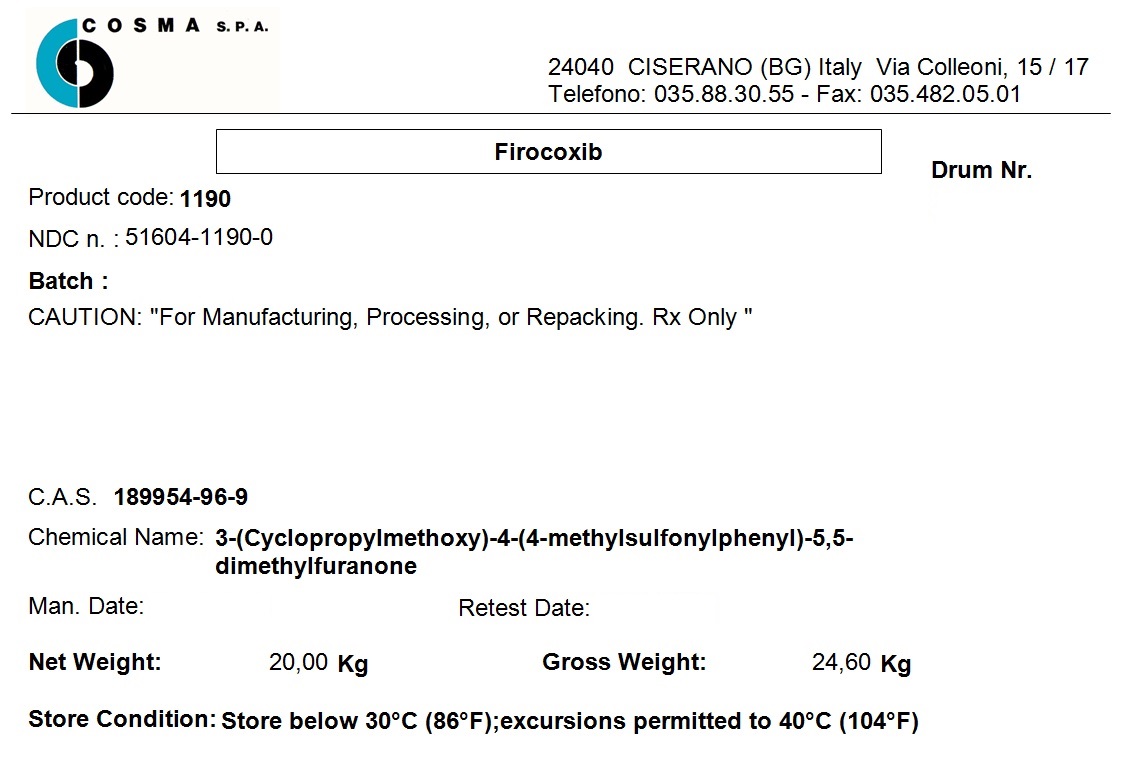 DRUG LABEL: Firocoxib
NDC: 51604-1190 | Form: POWDER
Manufacturer: COSMA SpA
Category: other | Type: BULK INGREDIENT - ANIMAL DRUG
Date: 20231114

ACTIVE INGREDIENTS: FIROCOXIB 20 kg/20 kg

Firocoxib

PACKAGE LABEL

COSMA S.p.A.

Via Colleoni, 15/17

24040 CISERANO (BG) Italy

Telefono: 035.88.30.55

Firocoxib

NDC n: 51604-1190-0

Batch:

CAUTION: "For Manufacturing, Processing, or Repacking. Rx Only"

C.A.S. 189954-96-9

Chemical Name: 3-(Cyclopropylmethoxy)-4-(4-methylsulfonylphenyl)-5,5-dimethylfuranone

Store Condition: Store below 30°C (86°F); excursions permitted to 40°C (104°F)